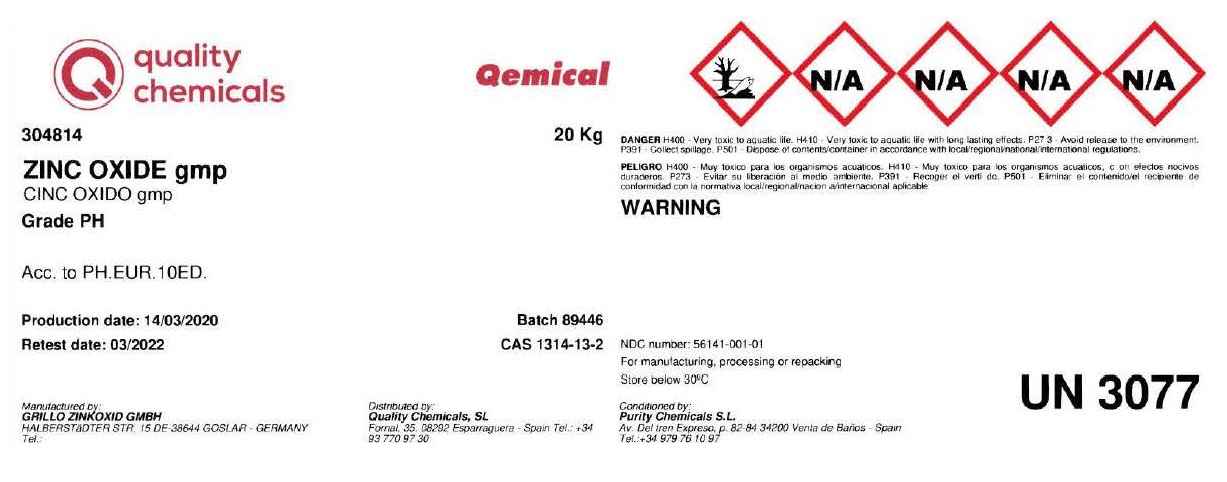 DRUG LABEL: Zinc Oxide
NDC: 56141-001 | Form: POWDER
Manufacturer: Quality Chemicals S.L.
Category: other | Type: BULK INGREDIENT - ANIMAL DRUG
Date: 20211130

ACTIVE INGREDIENTS: ZINC OXIDE 1 kg/1 kg

Zinc Oxide